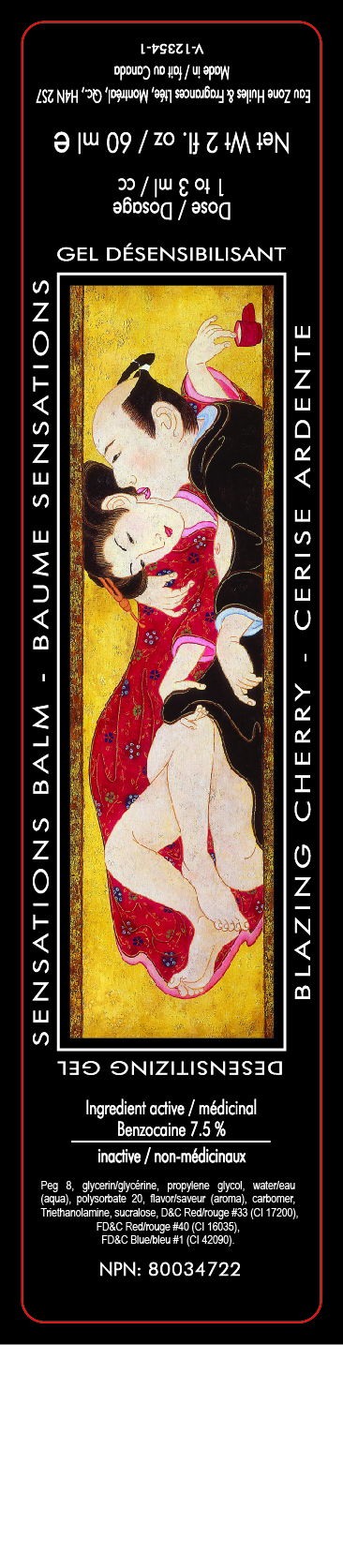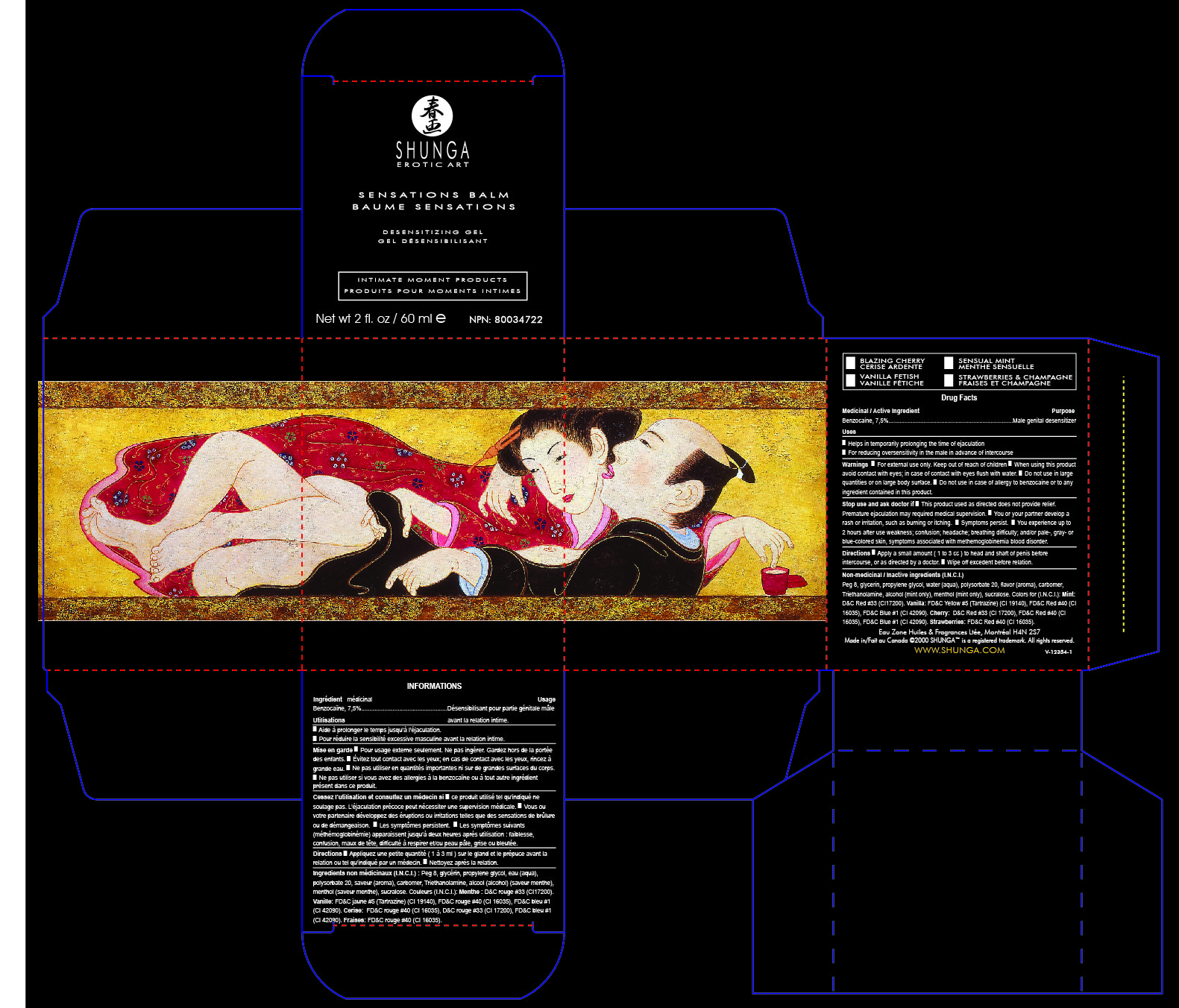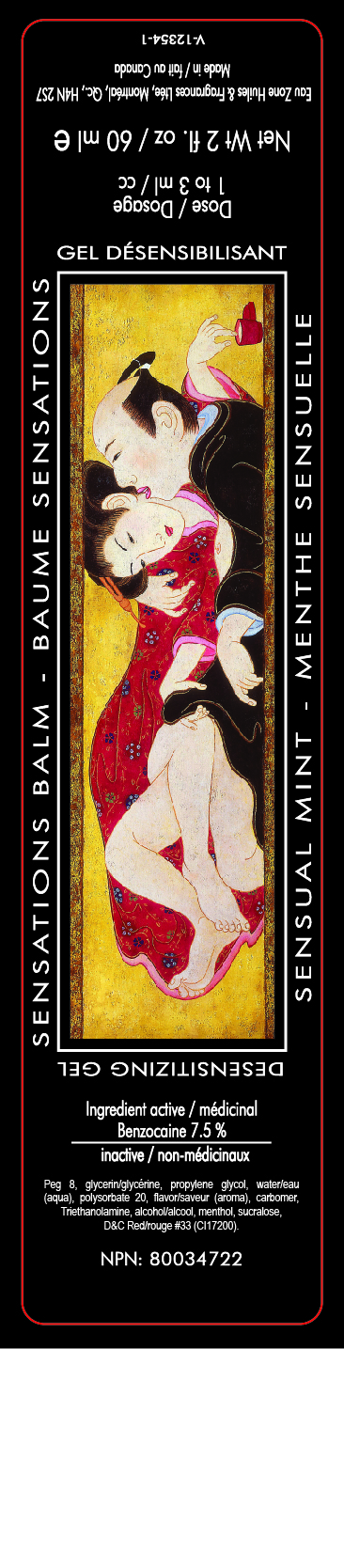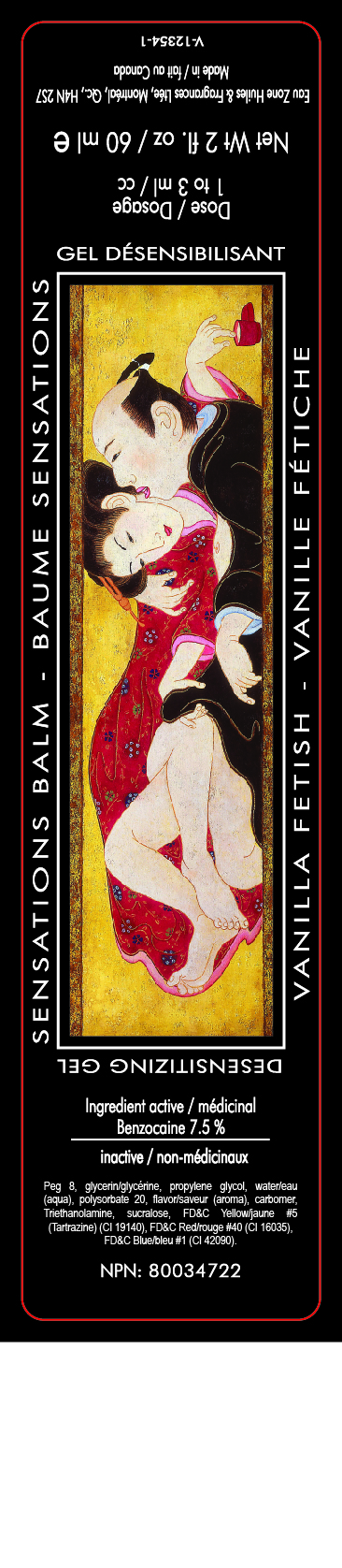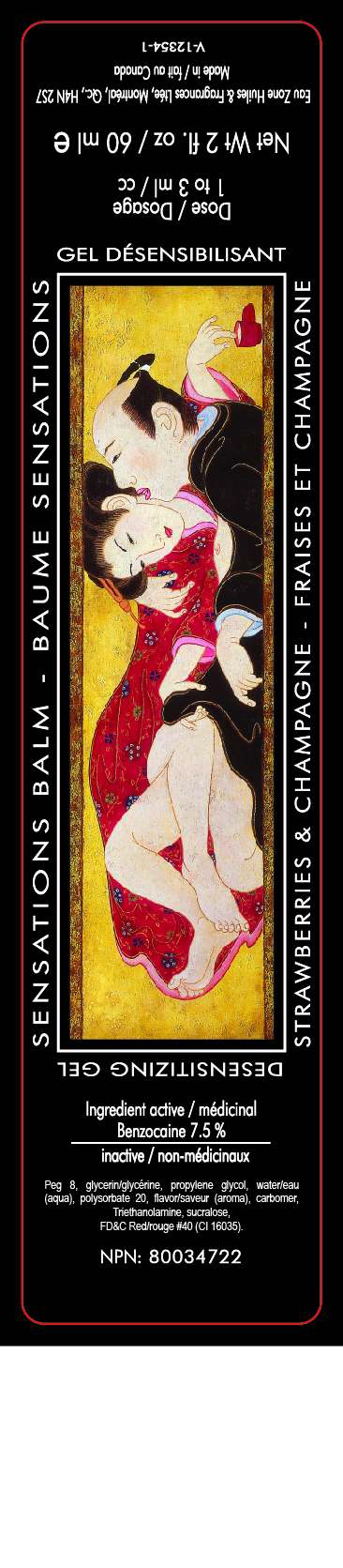 DRUG LABEL: Shunga
NDC: 63240-5000 | Form: GEL
Manufacturer: Eau Zone Oils and Fragrances LTD
Category: otc | Type: HUMAN OTC DRUG LABEL
Date: 20221109

ACTIVE INGREDIENTS: BENZOCAINE 5.07 g/67.5 g
INACTIVE INGREDIENTS: POLYETHYLENE GLYCOL 400 18 g/67.5 g; GLYCERIN 20.86 g/67.5 g; PROPYLENE GLYCOL 15 g/67.5 g; WATER 5.4 g/67.5 g; POLYSORBATE 20 0.66 g/67.5 g; CARBOMER 940 0.357 g/67.5 g; TROLAMINE 0.287 g/67.5 g; SUCRALOSE 0.006 g/67.5 g; D&C RED NO. 33 0.0027 g/67.5 g; FD&C RED NO. 40 0.0003 g/67.5 g; FD&C BLUE NO. 1 0.0001 g/67.5 g

Drug Facts

Active ingredient

Male Desensitizing Gel

Gel désensibilisant mâle

Active Ingredient
Benzocaine 7.5 pourcentage

Genital Desensitizer
Désensibilisant Genital
Benzocaine USP 7.5 pourcent
60ml

Warnings

■ For external use only. Keep out of reach of children ■ When using this product
avoid contact with eyes; in case of contact with eyes flush with water. ■ Do not use in large
quantities or on large body surface. ■ Do not use in case of allergy to benzocaine or to any
ingredient contained in this product.

Directions

Directions ■ Apply a small amount (1 to 3 cc) to head and shaft of penis before
intercourse, or as directed by a doctor. ■ Wipe off excedent before relation.

Stop use and ask doctor if ■ This product used as directed does not provide relief.
Premature ejaculation may required medical supervision. ■ You or your partner develop a
rash or irritation, such as burning or itching. ■ Symptoms persist. ■ You experience up to
2 hours after use weakness; confusion; headache; breathing difficulty; and/or pale-, gray- or
blue-colored skin, symptoms associated with methemoglobinemia blood disorder.

Warning

Warnings

For external use only. Keep out of reach of children

When using this product avoid contact with eyes; in case of contact with eyes flush with water.

Do not use in large quantities or on large body surface.

Do not use in case of allergy to benzocaine or to any ingredient contained in this product.

Purpose

Name: SHUNGA Sensation Balm

SHUNGA Male Genital Desensitizer helps in temporarily prolonging the time until ejaculation by diminishing tactile sensations to the penis.
Purpose
Male genital desensitizer
Uses
Helps in temporarily prolonging the time of ejaculation ■ For reducing oversensitivity in the male in advance of intercourse

Directions ■ Apply a small amount (1 to 3 cc) to head and shaft of penis before
intercourse, or as directed by a doctor. ■ Wipe off excedent before relation.

Non-medicinal / Inactive ingredients (I.N.C.I.)

Water (aqua), peg 8, glycerin, propylene glycol, triethanolamine, carbomer, flavor (aroma),
sucralose. Colors for (I.N.C.I.): Mint : D&C Red #33 (CI17200). Vanilla: FD&C Yellow #5
(Tartrazine) (CI 19140), FD&C Red #40 (CI 16035), FD&C Blue #1 (CI 42090). Cherry and
Strawberries: FD&C Red #40 (CI 16035), D&C Red #33 (CI 17200).

Eau Zone Huiles & Fragrances Ltée, Montréal H4N 2S7
Made in/Fait au Canada ©2000 SHUNGA™ is a registered trademark. All rights reserved.

Directions

■ Apply a small amount (1 to 3 cc) to head and shaft of penis before
intercourse, or as directed by a doctor. ■ Wipe off excedent before relation.